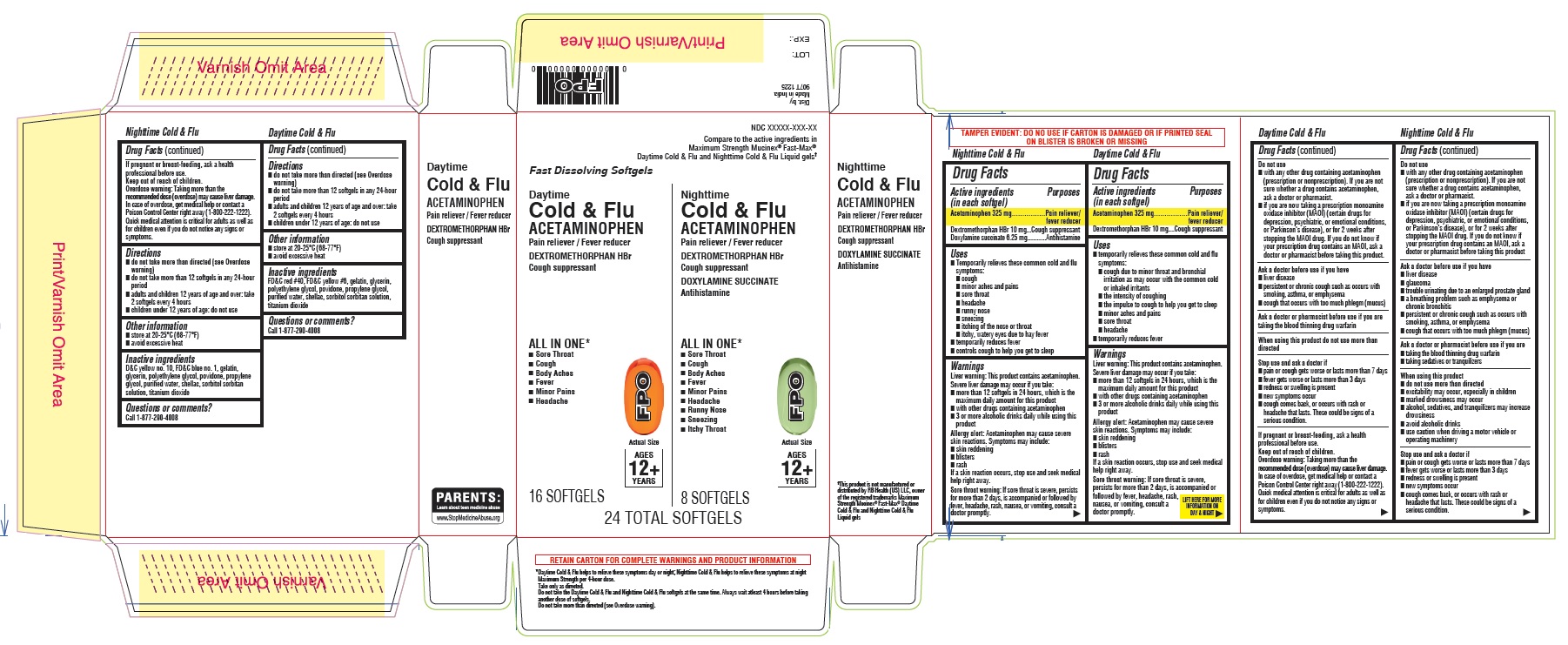 DRUG LABEL: Daytime Cold and Flu and Nighttime Softgels
NDC: 51316-937 | Form: KIT | Route: ORAL
Manufacturer: CVS Pharmacy
Category: otc | Type: HUMAN OTC DRUG LABEL
Date: 20260129

ACTIVE INGREDIENTS: DEXTROMETHORPHAN HYDROBROMIDE 10 mg/1 1; ACETAMINOPHEN 325 mg/1 1; DOXYLAMINE SUCCINATE 6.25 mg/1 1; ACETAMINOPHEN 325 mg/1 1; DEXTROMETHORPHAN HYDROBROMIDE 10 mg/1 1
INACTIVE INGREDIENTS: SORBITOL SOLUTION; GELATIN, UNSPECIFIED; SHELLAC; POVIDONE, UNSPECIFIED; GLYCERIN; SORBITAN; FD&C RED NO. 40; PROPYLENE GLYCOL; TITANIUM DIOXIDE; POLYETHYLENE GLYCOL, UNSPECIFIED; FD&C YELLOW NO. 6; WATER; POLYETHYLENE GLYCOL, UNSPECIFIED; GLYCERIN; FD&C BLUE NO. 1; PROPYLENE GLYCOL; WATER; POVIDONE, UNSPECIFIED; SHELLAC; GELATIN, UNSPECIFIED; SORBITAN; TITANIUM DIOXIDE; SORBITOL SOLUTION; D&C YELLOW NO. 10

CVS 907T Daytime Cold and Flu and Nighttime Softgels

Daytime Cold & Flu Softgels

Drug Facts

Active ingredients (in each softgel)

Acetaminophen 325 mg

Dextromethorphan HBr 10 mg

Purposes

Pain reliever/fever reducer

Cough suppressant

Uses

- temporarily relieves these common cold and flu symptoms:

- cough due to minor throat and bronchial irritation as may occur with the common cold or inhaled irritants

- the intensity of coughing

- the impulse to cough to help you get to sleep

- minor aches and pains

- sore throat

- headache

- temporarily reduces fever

Warnings

Liver warning: This product contains acetaminophen. Severe liver damage may occur if you take:

- more than 12 softgels in 24 hours, which is the maximum daily amount for this product
- with other drugs containing acetaminophen
- 3 or more alcoholic drinks daily while using this product

Allergy alert: Acetaminophen may cause severe skin reactions. Symptoms may include:

- skin reddening
- blisters
- rash

If a skin reaction occurs, stop use and seek medical help right away.

Sore throat warning: If sore throat is severe, persists for more than 2 days, is accompanied or followed by fever, headache, rash, nausea, or vomiting, consult a doctor promptly.

Do not use

- with any other drug containing acetaminophen (prescription or nonprescription). If you are not sure whether a drug contains acetaminophen, ask a doctor or pharmacist.
- if you are now taking a prescription monoamine oxidase inhibitor (MAOI) (certain drugs for depression, psychiatric, or emotional conditions, or Parkinson’s disease), or for 2 weeks after stopping the MAOI drug. If you do not know if your prescription drug contains an MAOI, ask a doctor or pharmacist before taking this product.

Ask a doctor before use if you have

- liver disease
- persistent or chronic cough such as occurs with smoking, asthma, or emphysema
- cough that occurs with too much phlegm (mucus)

Ask a doctor or pharmacist before use if you are taking the blood thinning drug warfarin

When using this product do not use more than directed

Stop use and ask a doctor if

- pain or cough gets worse or lasts more than 7 days
- fever gets worse or lasts more than 3 days
- redness or swelling is present
- new symptoms occur
- cough comes back or occurs with rash or headache that lasts. These could be signs of a serious condition.

PREGNANCY OR BREAST FEEDING

If pregnant or breast-feeding, ask a health professional before use

Keep out of reach of children.

Overdose warning: Taking more than the recommended dose (overdose) may cause liver damage. In case of overdose, get medical help or contact a Poison Control Center right away (1-800-222-1222). Quick medical attention is critical for adults as well as for children even if you do not notice any signs or symptoms.

Directions

- do not take more than directed (see Overdose warning)
- do not take more than 12 softggels in any 24-hour period
- adults and children 12 years of age and over: take 2 softgels every 4 hours
- children under 12 years of age: do not use

Other information

- store at 20-25°C (68-77°F)
- avoid excessive heat

Inactive ingredients

FD&C blue no. 1, gelatin, polyethylene glycol, povidone, propylene glycol, purified water, shellac, sorbitol sorbitan solution, titanium dioxide

Questions or comments? Call 1-877-290-4008

Nighttime Cold & Flu Softgels

Drug Facts

Active ingredients (in each softgel)

Acetaminophen 325 mg

Dextromethorphan HBr 10 mg

Doxylamine succinate 6.25 mg

Purposes

Pain reliever/fever reducer

Cough suppressant

Antihistamine

Uses

- temporarily relieves these common cold and flu symptoms:

- cough
- minor aches and pains
- sore throat
- headache
- runny nose
- sneezing
- itching of the nose or throat
- itchy, watery eyes due to hay fever

- temporarily reduces fever
- controls cough to help you get to sleep

Warnings

Liver warning: This product contains acetaminophen. Severe liver damage may occur if you take:

- more than 12 softgels in 24 hours, which is the maximum daily amount for this product
- with other drugs containing acetaminophen
- 3 or more alcoholic drinks daily while using this product

Allergy alert: Acetaminophen may cause severe skin reactions. Symptoms may include:

- skin reddening
- blisters
- rash

If a skin reaction occurs, stop use and seek medical help right away.

Sore throat warning: If sore throat is severe, persists for more than 2 days, is accompanied or followed by fever, headache, rash, nausea, or vomiting, consult a doctor promptly.

Do not use

- with any other drug containing acetaminophen (prescription or nonprescription). If you are not sure whether a drug contains acetaminophen, ask a doctor or pharmacist.
- if you are now taking a prescription monoamine oxidase inhibitor (MAOI) (certain drugs for depression, psychiatric, or emotional conditions, or Parkinson’s disease), or for 2 weeks after stopping the MAOI drug. If you do not know if your prescription drug contains an MAOI, ask a doctor or pharmacist before taking this product.

Ask a doctor before use if you have

- liver disease
- glaucoma
- trouble urinating due to an enlarged prostate gland
- a breathing problem such as emphysema or chronic bronchitis
- persistent or chronic cough such as occurs with smoking, asthma, or emphysema
- cough that occurs with too much phlegm (mucus)

Ask a doctor or pharmacist before use if you are

- taking the blood thinning drug warfarin
- taking sedatives or tranquilizers

When using this product

- do not use more than directed
- excitability may occur, especially in children
- marked drowsiness may occur
- alcohol, sedatives, and tranquilizers may increase drowsiness
- avoid alcoholic drinks
- use caution when driving a motor vehicle or operating machinery

Stop use and ask a doctor if

- pain or cough gets worse or lasts more than 7 days
- fever gets worse or lasts more than 3 days
- redness or swelling is present
- new symptoms occur
- cough comes back or occurs with rash or headache that lasts. These could be signs of a serious condition.

PREGNANCY OR BREAST FEEDING

If pregnant or breast-feeding, ask a health professional before use.

Keep out of reach of children.

Overdose warning: Taking more than the recommended dose (overdose) may cause liver damage. In case of overdose, get medical help or contact a Poison Control Center right away (1-800-222-1222). Quick medical attention is critical for adults as well as for children even if you do not notice any signs or symptoms.

Directions

- do not take more than directed (see Overdose warning)
- do not take more than 12 softgels in any 24-hour period
- adults and children 12 years of age and over: take 2 softgels every 4 hours
- children under 12 years of age: do not use

Other information

- store at 20-25°C (68-77°F)
- avoid excessive heat

Inactive ingredients

D&C yellow no. 10, FD&C blue no. 1, gelatin, glycerin, polyethylene glycol, povidone, propylene glycol, purified water, shellac, sorbitol sorbitan solution, titanium dioxide

Questions or comments? Call 1-877-290-4008